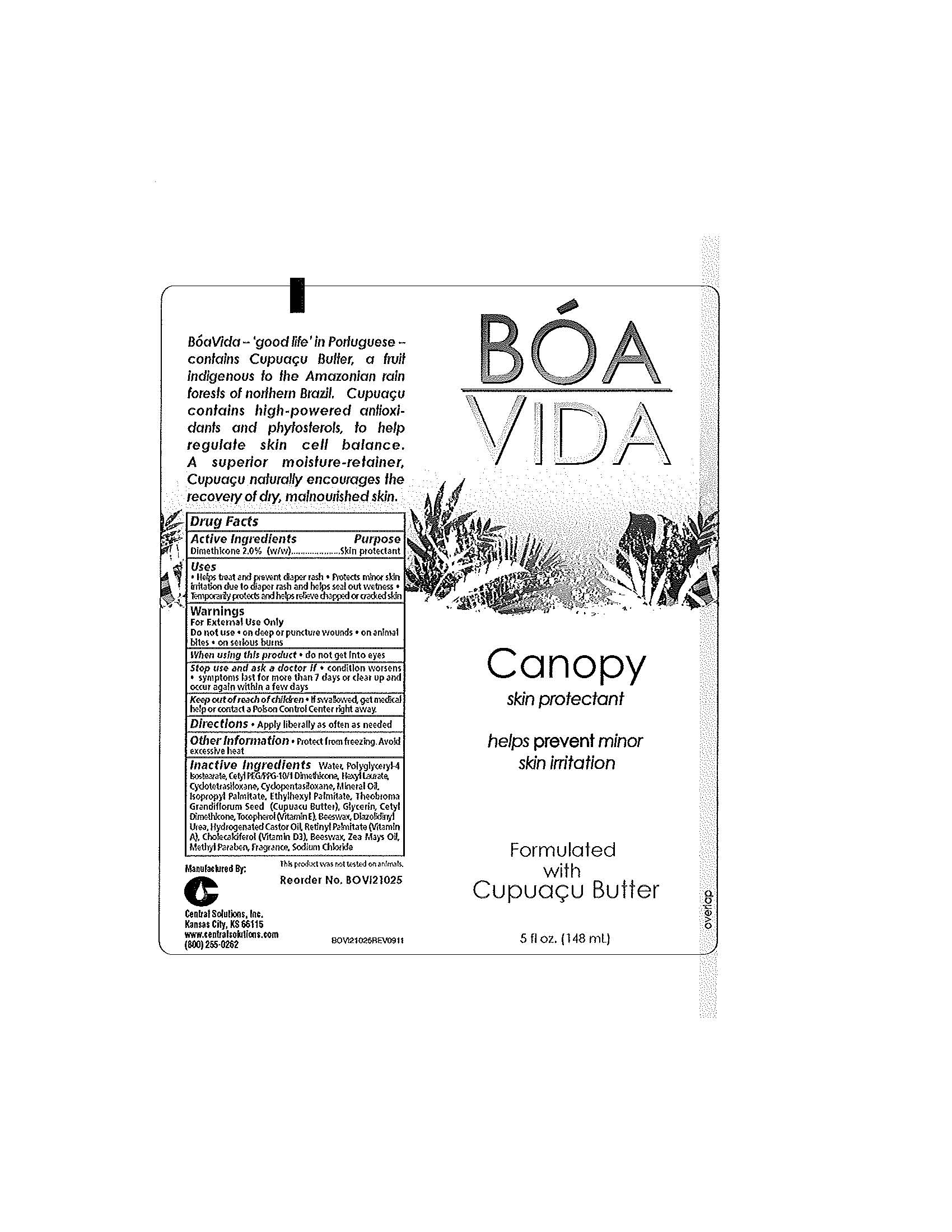 DRUG LABEL: BOA VIDA Canopy
NDC: 62654-144 | Form: CREAM
Manufacturer: Central Solutions Inc
Category: otc | Type: HUMAN OTC DRUG LABEL
Date: 20241209

ACTIVE INGREDIENTS: DIMETHICONE 2 g/100 mL
INACTIVE INGREDIENTS: WATER; POLYGLYCERYL-4 ISOSTEARATE; HEXYL LAURATE; QUADROSILAN; CYCLOMETHICONE 5; MINERAL OIL; ISOPROPYL PALMITATE; ETHYLHEXYL PALMITATE; THEOBROMA GRANDIFLORUM SEED; GLYCERIN; TOCOPHEROL; YELLOW WAX; DIAZOLIDINYL UREA; HYDROGENATED CASTOR OIL; VITAMIN A PALMITATE; CHOLECALCIFEROL; CORN OIL; METHYLPARABEN; SODIUM CHLORIDE

Drug Facts 62654-144

Active Ingredients

Dimethicone 2.0% (w/w)

Purpose

Skin protectant

Uses

Helps treat and prevent diaper rash

Protects minor skin irritation due to diaper rash and helps seal out wetness

Temporarily protects and helps relieve chapped or cracked skin

Warnings

For External Use Only

Do not use

on deep or puncture wounds

on animal bites

on serious burns

When using this product

do not get into eyes

Stop use and ask a doctor if

condition worsens

symptoms last for more than 7 days or clear up and occur again within a few days

Keep out of reach of children

If swallowed, get medical help or contact a Poison Control Center right away.

Directions

Apply liberally as often as needed

Other Information

Protect from freezing.

Avoid excessive heat

Inactive Ingredients

Water, Polyglyceryl-4 Isostearate, Cetyl PEG/PPG-10/1 Dimethicone, Hexyl Laurate,Cyclotetrasiloxane, Cyclopentasiloxane, Mineral Oil, Isopropyl Palmitate, Ethylhexyl Palmitate, Theobroma Grandiflorum Seed (Cupuacu Butter), Glycerin, Cetyl Dimethicone, Tocopherol (Vitamin E), Beeswax, Diazolidinyl Urea, Hydrogenated Castor Oil, Retinyl Palmitate (Vitamin A), Cholecalciferol (Vitamin D3), Beeswax, Zea Mays Oil, Methyl Paraben, Fragrance, Sodium Chloride

PACKAGE LABEL

BOA

VIDA

Canopy

skin protectant

helps prevent minor

skin irritation

Formulated

with

Cupuacu Butter

5 fl oz. (148 mL)